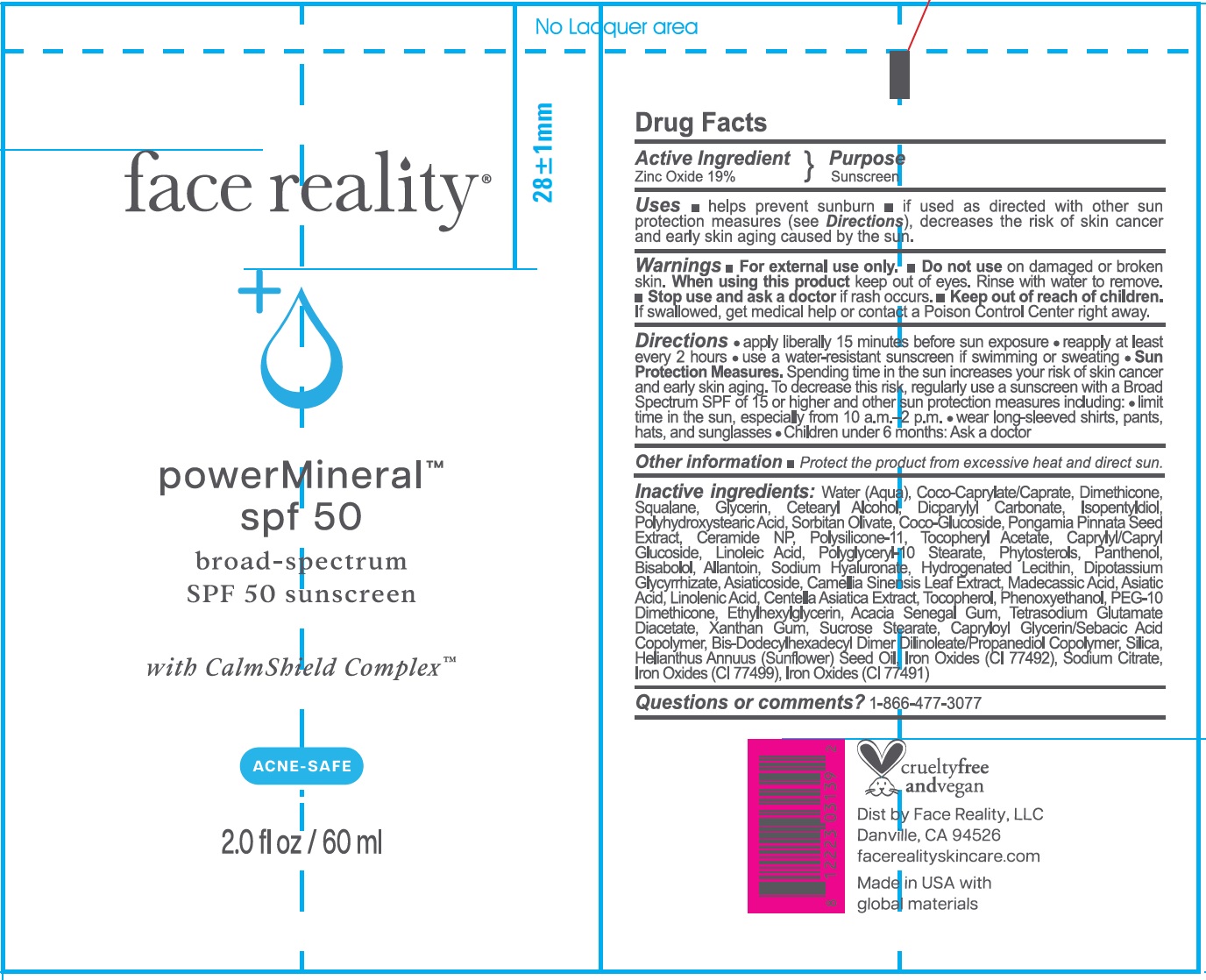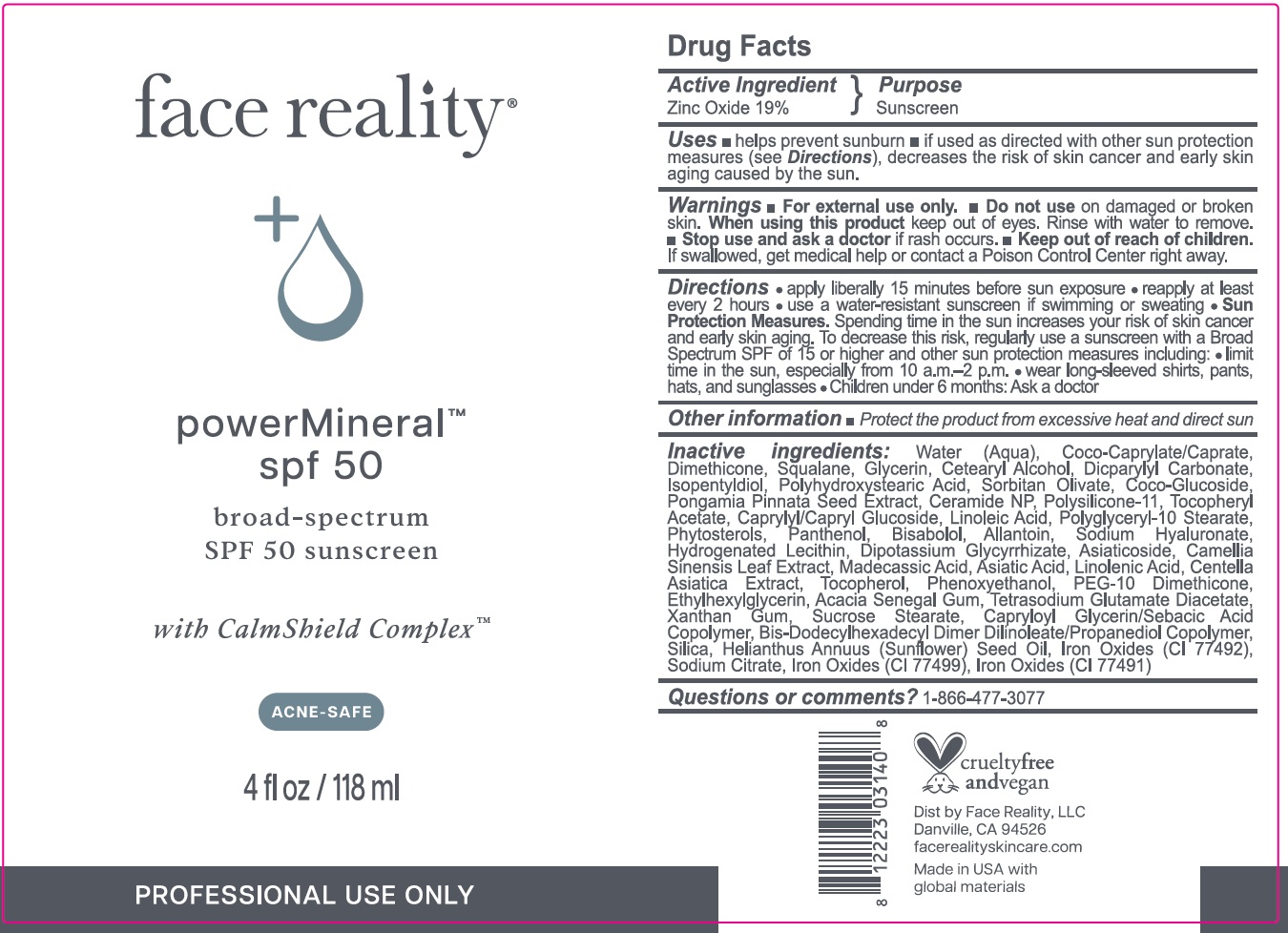 DRUG LABEL: Face Reality Power Mineral Sunscreen SPF 50
NDC: 70707-456 | Form: CREAM
Manufacturer: Face Reality, LLC
Category: otc | Type: HUMAN OTC DRUG LABEL
Date: 20250729

ACTIVE INGREDIENTS: ZINC OXIDE 190 mg/1 mL
INACTIVE INGREDIENTS: BIS-DODECYLHEXADECYL DIMER DILINOLEATE/PROPANEDIOL COPOLYMER; WATER; COCOYL CAPRYLOCAPRATE; DIMETHICONE; SQUALANE; GLYCERIN; CETEARYL ALCOHOL; DICAPRYLYL CARBONATE; ISOPENTYLDIOL; SORBITAN OLIVATE; COCO-GLUCOSIDE; PONGAMIA PINNATA SEED; CERAMIDE NP; DIMETHICONE/VINYL DIMETHICONE CROSSPOLYMER (SOFT PARTICLE); .ALPHA.-TOCOPHEROL ACETATE; CAPRYLYL/CAPRYL OLIGOGLUCOSIDE; LINOLEIC ACID; POLYGLYCERYL-10 STEARATE; PANTHENOL; BISABOLOL; ALLANTOIN; HYALURONATE SODIUM; HYDROGENATED SOYBEAN LECITHIN; DIPOTASSIUM GLYCYRRHIZATE; ASIATICOSIDE; GREEN TEA LEAF; MADECASSIC ACID; ASIATIC ACID; LINOLENIC ACID; CENTELLA ASIATICA TRITERPENOIDS; TOCOPHEROL; PHENOXYETHANOL; ETHYLHEXYLGLYCERIN; ACACIA SENEGAL GUM; TETRASODIUM GLUTAMATE DIACETATE; XANTHAN GUM; SUCROSE STEARATE; SILICON DIOXIDE; SUNFLOWER OIL; FERRIC OXIDE YELLOW; SODIUM CITRATE; FERROSOFERRIC OXIDE; FERRIC OXIDE RED; PEG-10 DIMETHICONE (400 CST); CAPRYLOYL GLYCERIN/SEBACIC ACID COPOLYMER (2000 MPA.S); BETA-SITOSTEROL; POLYHYDROXYSTEARIC ACID (2300 MW)

Face Reality Power Mineral Sunscreen SPF 50

Active Ingredient

Zinc Oxide 19%

Purpose

Sunscreen

Uses

- helps prevent sunburn
- if used as directed with other sun protection measures (see Directions), decreases the risk of skin cancer and early skin aging caused by the sun.

Warnings

For external use only.

Do not use

- on damaged or broken skin.

When using this product

keep out of eyes. Rinse with water to remove.

Stop use and ask a doctor

- if rash occurs.

Keep out of reach of children.

- If swallowed, get medical help or contact a Poison Control Center right away.

Directions

- apply liberally 15 minutes before sun exposure
- reapply at least every 2 hours
- use a water-resistant sunscreen if swimming or sweating
- Sun Protection Measures.Spending time in the sun increases your risk of skin cancer and early skin aging. To decrease this risk, regularly use a sunscreen with a Broad Spectrum SPF of 15 or higher and other sun protection measures including:
- limit time in the sun, especially from 10 a.m.-2 p.m.
- wear long-sleeved shirts, pants, hats, and sunglasses
- Children under 6 months: Ask a doctor

Other information

- Protect the product from excessive heat and direct sun.

Inactive ingredients:

Water (Aqua), Coco-Caprylate/Caprate, Dimethicone, Squalane, Glycerin, Cetearyl Alcohol, Dicaprylyl Carbonate, Isopentyldiol, Polyhydroxystearic Acid, Sorbitan Olivate, Coco-Glucoside, Pongamia Pinnata Seed Extract, Ceramide NP, Polysilicone-11, Tocopheryl Acetate, Caprylyl/Capryl Glucoside, Linoleic Acid, Polyglyceryl 10 Stearate, Phytosterols, Panthenol, Bisabolol, Allantoin, Sodium Hyaluronate, Hydrogenated Lecithin, Dipotassium Glycyrrhizate, Asiaticoside, Camellia Sinensis Leaf Extract, Madecassic Acid, Asiatic Acid, Linolenic Acid, Centella Asiatica Extract, Tocopherol, Phenoxyethanol, PEG-10 Dimethicone, Ethylhexylglycerin, Acacia Senegal Gum, Tetrasodium Glutamate Diacetate, Xanthan Gum, Sucrose Stearate, Capryloyl Glycerin/Sebacic Acid Copolymer, Bis-Dodecylhexadecyl Dimer Dilinoleate/Propanediol Copolymer, Silica, Helianthus Annuus (Sunflower) Seed Oil, Iron Oxides (CI 77492), Sodium Citrate, Iron Oxides (CI 77499), Iron Oxides (CI 77491)

Questions or comments?

1-866-477-3077